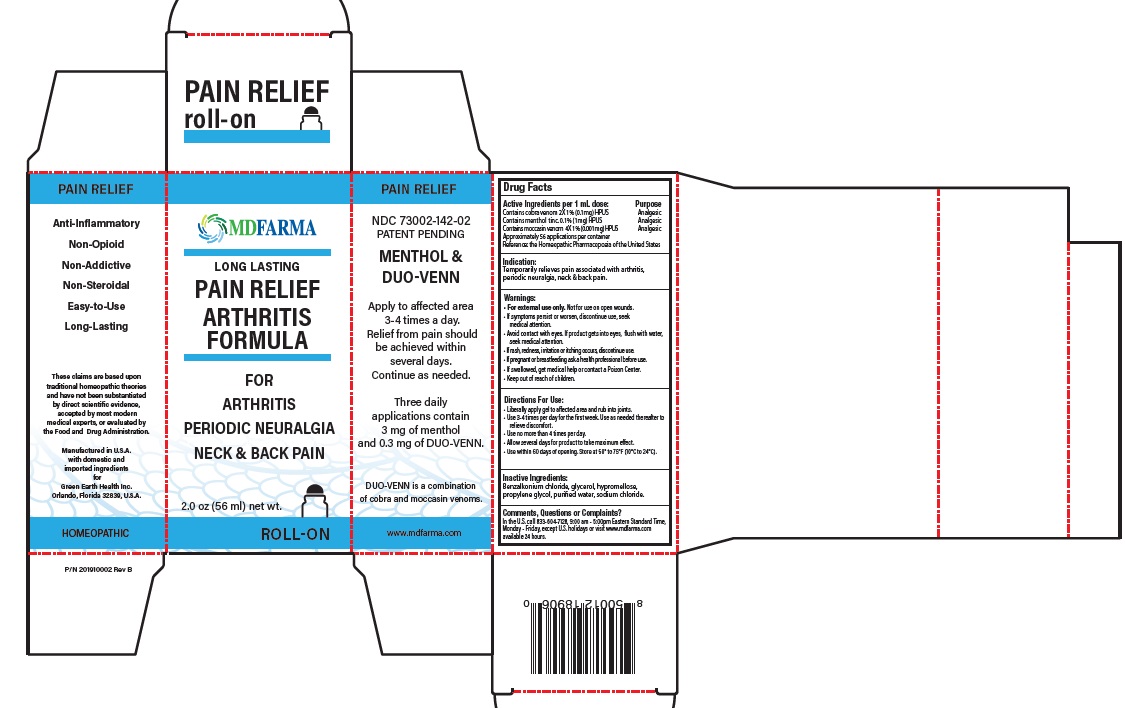 DRUG LABEL: PAIN RELIEF MENTHOL AND SNAKE VENOM
NDC: 73002-142 | Form: GEL
Manufacturer: Green Earth Health Inc.
Category: homeopathic | Type: HUMAN OTC DRUG LABEL
Date: 20250722

ACTIVE INGREDIENTS: NAJA NAJA VENOM 0.1 mg/1 mL; MENTHOL, (+)- 1 mg/1 mL; AGKISTRODON PISCIVORUS VENOM 0.001 mg/1 mL
INACTIVE INGREDIENTS: BENZALKONIUM CHLORIDE; GLYCERIN; HYPROMELLOSE, UNSPECIFIED; PROPYLENE GLYCOL; WATER; SODIUM CHLORIDE

Drug Facts

Active Ingredients Purpose

Cobra venom (Naja naja) 2X 1% (0.1mg) HPUS Analgesic
Menthol (Mentholum) Tinc. 0.1% (1mg) HPUS Analgesic
Moccasin venom (A.piscivorus) 4X 1%(0.001mg) HPUS Analgesic

Approximately 56 applications per container

Reference: the Homeopathic Pharmacopoeia of the United States (HPUS)

Indication:

Temporarily relieves pain associated with arthritis, periodic neuralgia, neck & back pain

Warnings:

• For external use only.Not for use on open wounds.
• If symptoms persist or worsen, discontinue use, seek medical attention.
• Avoid contact with eyes. If product gets into eyes, flush with water, seek medical attention.
• If rash, redness, irritation or itching occurs, discontinue use.
• If pregnant or breastfeeding ask a health professional before use.
• If swallowed, get medical help or contact a Poison Center.
• Keep out of reach of children.

Directions For Use:

- Liberally apply gel to affected area and rub into joints.
- Use 3-4 times per day for the first week. Use as needed thereafter to relieve discomfort.
- Use no more than 4 times per day.
- Allow several days for product to take maximum effect.
- Use within 60 days from opening. Store at 50° to 75°F (10°C to 24°C)

Inactive Ingredients:

Benzalkonium chloride, glycerol, hypromellose, propylene glycol, purified water, sodium chloride.